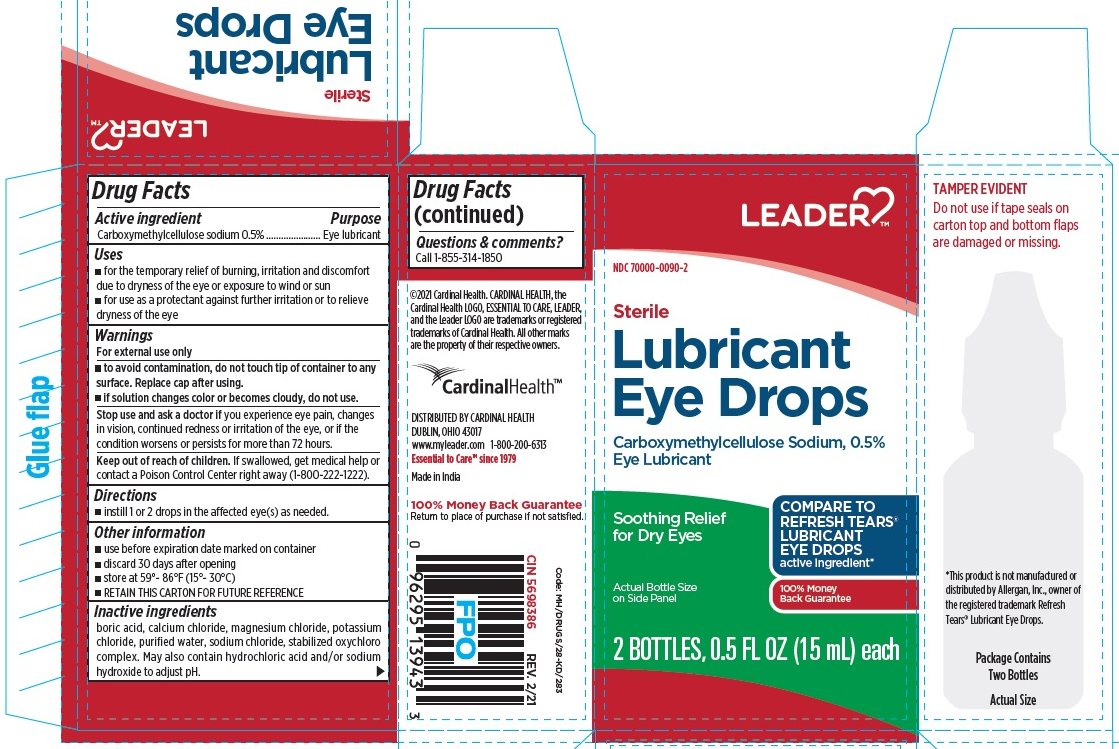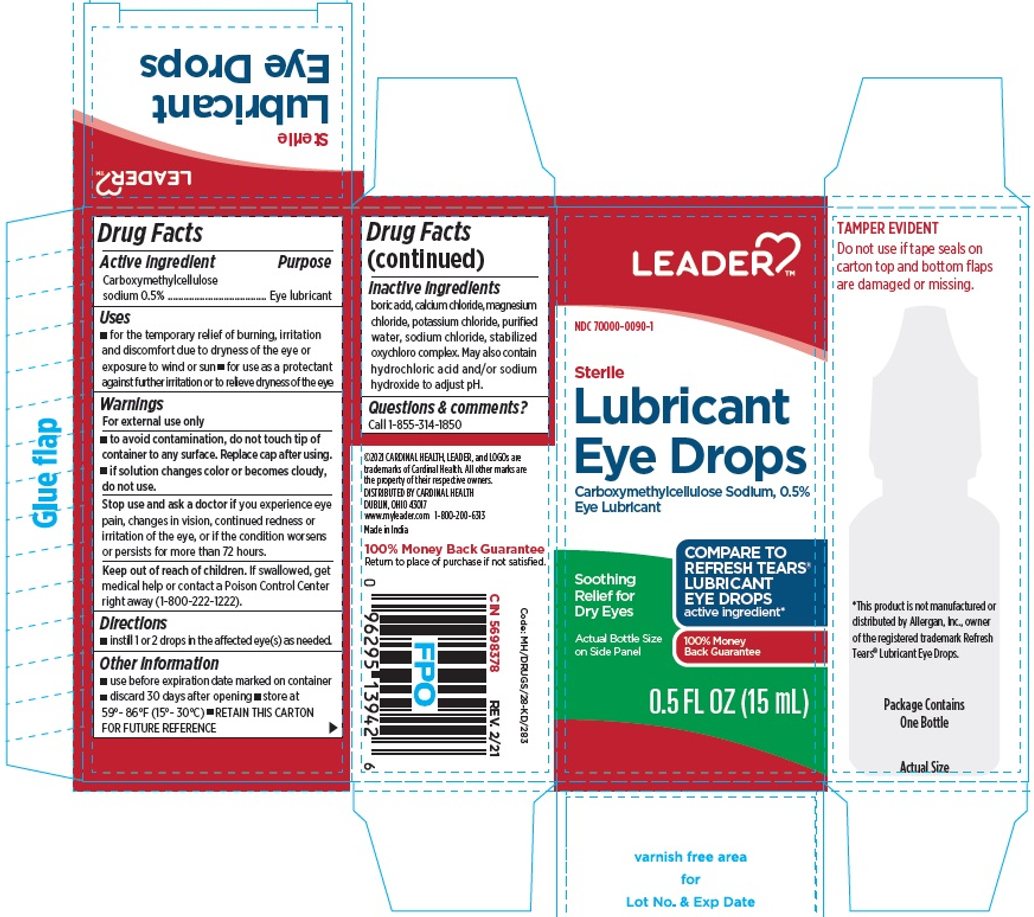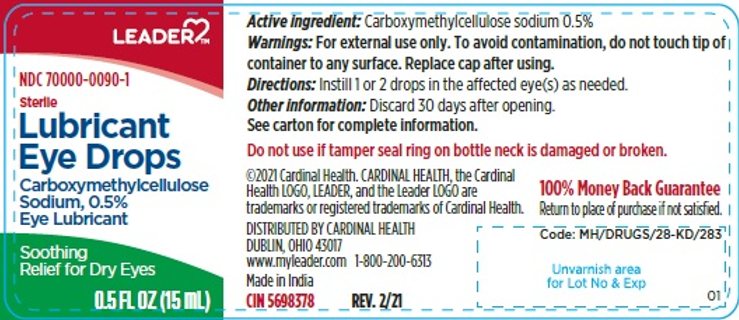 DRUG LABEL: Lubricant Drops
NDC: 70000-0090 | Form: SOLUTION/ DROPS
Manufacturer: CARDINAL HEALTH 110, LLC. DBA LEADER
Category: otc | Type: HUMAN OTC DRUG LABEL
Date: 20250912

ACTIVE INGREDIENTS: CARBOXYMETHYLCELLULOSE SODIUM, UNSPECIFIED 5 mg/1 mL
INACTIVE INGREDIENTS: BORIC ACID; CALCIUM CHLORIDE; MAGNESIUM CHLORIDE; POTASSIUM CHLORIDE; WATER; SODIUM CHLORIDE; SODIUM CHLORITE

Sterile Lubricant Eye Drops

Active ingredient

Carboxymethylcellulose sodium 0.5%

Purpose

Eye lubricant

Uses

- For the temporary relief of burning, irritation, and discomfort due to dryness of the eye or exposure to wind or sun.
- For use as a protectant against further irritation or to relieve dryness of the eye.

Warnings

- For external use only.
- To avoid contamination, do not touch tip of container to any surface. Replace cap after using.
- If solution changes color or becomes cloudy, do not use.

Stop use and ask a doctor if

you experience eye pain, changes in vision, continued redness or irritation of the eye, or if the condition worsens or persists for more than 72 hours.

Keep out of reach of children.

If swallowed, get medical help or contact a Poison Control Center right away.

Directions

Instill 1 or 2 drops in the affected eye(s) as needed.

Other information

- Use only if imprinted tape seals on top and bottom flaps are intact and clearly legible.
- Use before expiration date marked on container.
- Discard 90 days after opening
- Store at 59°-86°F (15°-30°C).
- RETAIN THIS CARTON FOR FUTURE REFERENCE.

Inactive ingredients

Boric acid; calcium chloride; magnesium chloride; potassium chloride; purified water; stabilized oxychloro complex; and sodium chloride. May also contain hydrochloric acid and/or sodium hydroxide to adjust pH.

.

TAMPER EVIDENT

Do not use if tape seals on carton top and bottom flaps are damaged or missing.

*This product is not manufactured or distributed by Allergan, Inc., owner of the registered trademark

Refresh Tears® Lubricant Eye Drops.

DISTRIBUTED BY CARDINAL HEALT

DUBLIN, OHIO 43017

www.myleader.com 1-800-200-6313

Made in India

100% Money Back Guarantee

Return to place of purchase if not satisfied.

Code: MH/DRUGS/28-KD/283

CIN 5698378 | REV. 2/21
CIN 5698386 | REV. 2/21

Principal Display Panel

LEADER®

NDC 70000-0090-1

Sterile

Lubricant

Eye Drops

Carboxymethylcellulose

Sodium, 0.5%

Eye Lubricant

Soothing

Relief for Dry Eyes

0.5 FL OZ (15 mL)

Principal Display Panel

LEADER®

NDC 70000-0090-1

Sterile

Lubricant

Eye Drops

Carboxymethylcellulose Sodium, 0.5%

Eye Lubricant

Soothing Relief for Dry Eyes

Actual Bottle Size on Side Panel

COMPARE TO REFRESH TEARS® LUBRICANT EYE DROPS active ingredient*

100% Money Back Guarantee

0.5 FL OZ (15 mL)

Principal Display Panel

LEADER®

NDC 70000-0090-2

Sterile

Lubricant

Eye Drops

Carboxymethylcellulose Sodium, 0.5%

Eye Lubricant

Soothing Relief for Dry Eyes

Actual Bottle Size on Side Panel

COMPARE TO REFRESH TEARS® LUBRICANT EYE DROPS active ingredient*

100% Money Back Guarantee

2 BOTTLES, 0.5 FL OZ (15 mL) each